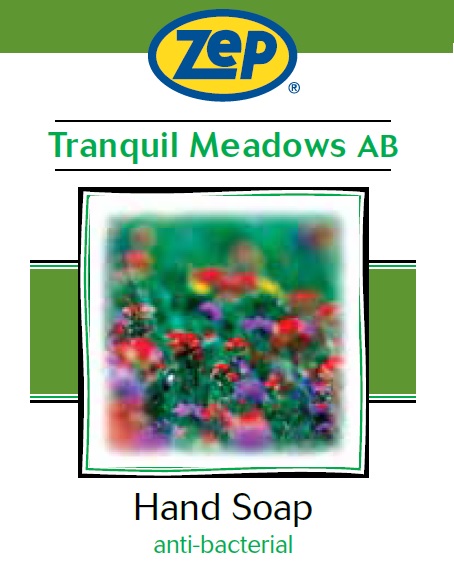 DRUG LABEL: Zep Tranq Mdw AB Foam
NDC: 66949-387 | Form: LIQUID
Manufacturer: Zep Inc.
Category: otc | Type: HUMAN OTC DRUG LABEL
Date: 20251226

ACTIVE INGREDIENTS: BENZALKONIUM CHLORIDE 0.13 g/100 mL
INACTIVE INGREDIENTS: METHYLISOTHIAZOLINONE; HEXANEDIOL; METHYLCHLOROISOTHIAZOLINONE; WATER; CETRIMONIUM CHLORIDE; GLYCERIN; PHENOXYETHANOL; IODOPROPYNYL BUTYLCARBAMATE; LAUROYL/MYRISTOYL AMIDOPROPYL AMINE OXIDE; FD&C BLUE NO. 1; FD&C YELLOW NO. 5; DI-PPG-2 MYRETH-10 ADIPATE; TETRASODIUM IMINODISUCCINATE; ANHYDROUS CITRIC ACID

66949-387 / 3387 Tranquil Meadows AB

Active Ingredient

Benzalkonium Chloride 0.13%

Purpose

Antibacterial Hand Wash

Uses

For hand washing to decrease bacteria on skin.

Warnings

For external use only. Do not use in the eyes; if in eyes, rinse promptly and thoroughly with water.

When using this product

- Do not swallow.
- If swallowed, do not induce vomiting and if individual is conscious, give large quantities of water to drink and consult a physician immediately

Stop use and ask a doctor if skin irritation or redness persists for more than 72 hours.

Keep out of reach of children and pets. Children must be supervised in use of this product.

Directions

- Wet hands with water.
- Massage soap into hands and wrists, emphasizing back of hands, knuckles and cuticles.
- Rinse thoroughly and dry.

Other information

- Store at 20 to 25°C (68 to 77°F).
- Dispose in accordance with all applicable federal, state and local regulations.

Inactive Ingredients

Water, Cetrimonium Chloride, Lauryl/Myristyl Amidopropyl Amine Oxide, Glycerin, Di-PPG-2 Myreth-10 Adipate, Fragrance, Phenoxyethanol, Iodopropynyl Butylcarbamate, Methylisothiazolinone, Hexanediol, Tetrasodium Iminodisuccinate, Methylchloroisothiazolinone, Citric Acid, Blue 1, Yellow 5

Questions or comments?

Call 1-877-I-BUY-ZEP (1-877-428-9937)